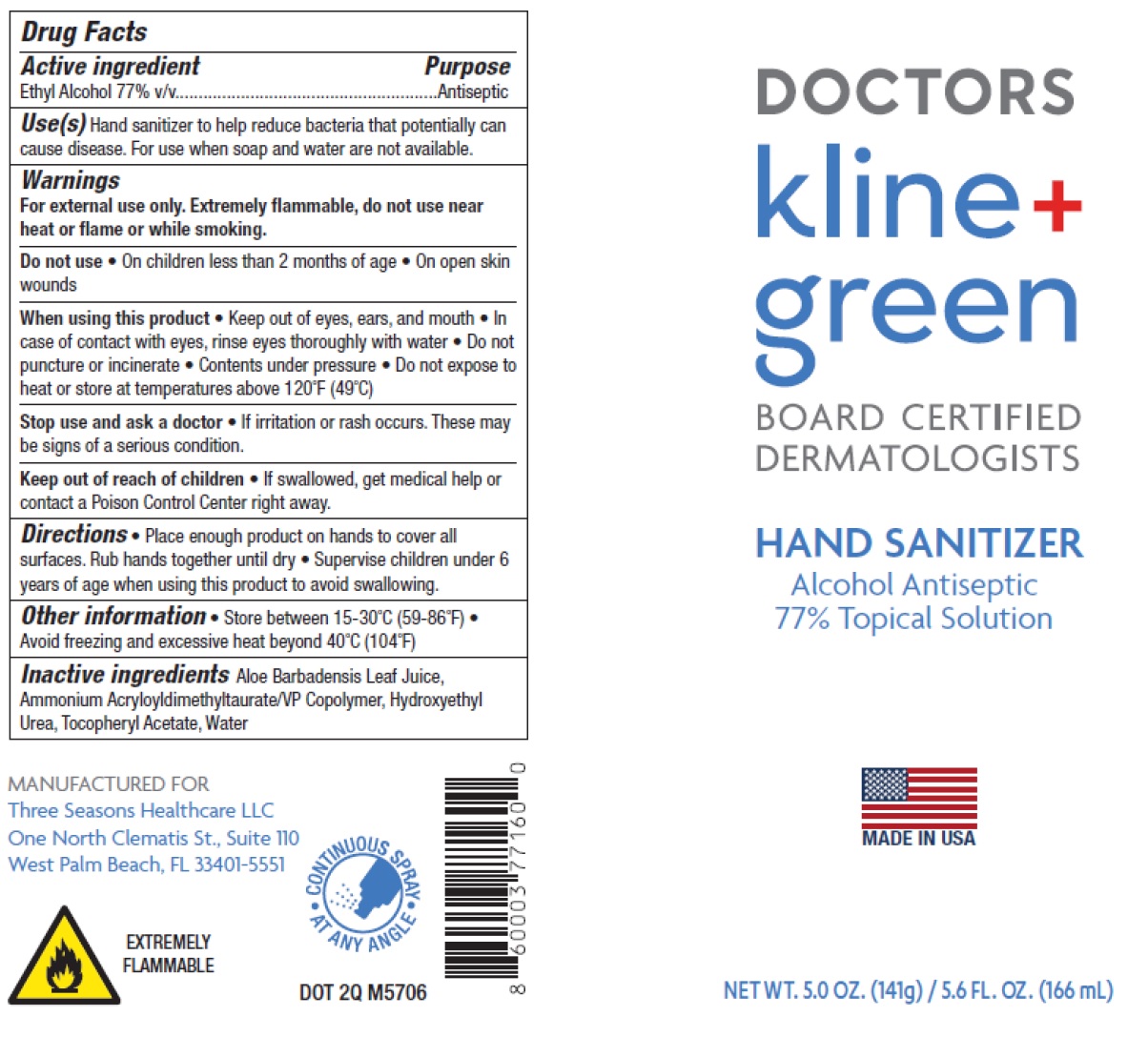 DRUG LABEL: Doctors Kline and Green Board Certified Dermatologist Hand Sanitizer Alcohol Antiseptic
NDC: 23667-102 | Form: LIQUID
Manufacturer: Formulated Solutions, LLC
Category: otc | Type: HUMAN OTC DRUG LABEL
Date: 20231129

ACTIVE INGREDIENTS: ALCOHOL 77 mL/100 mL
INACTIVE INGREDIENTS: ALOE VERA LEAF; AMMONIUM ACRYLOYLDIMETHYLTAURATE/VP COPOLYMER; HYDROXYETHYL UREA; .ALPHA.-TOCOPHEROL ACETATE; WATER

Doctors Kline & Green Board Certified Dermatologist Hand Sanitizer Alcohol Antiseptic

Active ingredient

Ethyl Alcohol 77% v/v

Purpose

Antiseptic

Uses(s)

Hand sanitizer to help reduce bacteria that potentially can cause disease. For use when soap and water are not available.

Warnings

For external use only. Extermely flammable, do not use near heat or flame or while smoking.

Do not use

- On children less than 2 months of age
- On open skin wounds

When using this product

- keep out of eyes, ears, and mouth
- In case of contact with eyes, rinse eyes thoroughly with water.
- Do not puncture or incinerate
- Contents under pressure
- Do not expose to heat or store at temperatures above 120°F (49°C)

Stop use and ask a doctor

- If irritation or rash occurs. These may be signs of a serious condition.

Keep out of reach of children.

If swallowed, get medical help or contact a Poison Control Center right away.

Directions

- Place enough product on hands to cover all surfaces. Rub hands together until dry
- Supervise children under 6 years of age when using this product to avoid swallowing.

Other information

- Store between 15-30°C (59-86°F)
- Avoid freezing and excessive heat beyond 40°C (104°F)

Inactive ingredients

Aloe Barbadensis Leaf Juice, Ammonium Acryloyldimethyltaurate/VP Copolymer, HYdroxyethyl Urea, Tocopheryl Acetate, Water